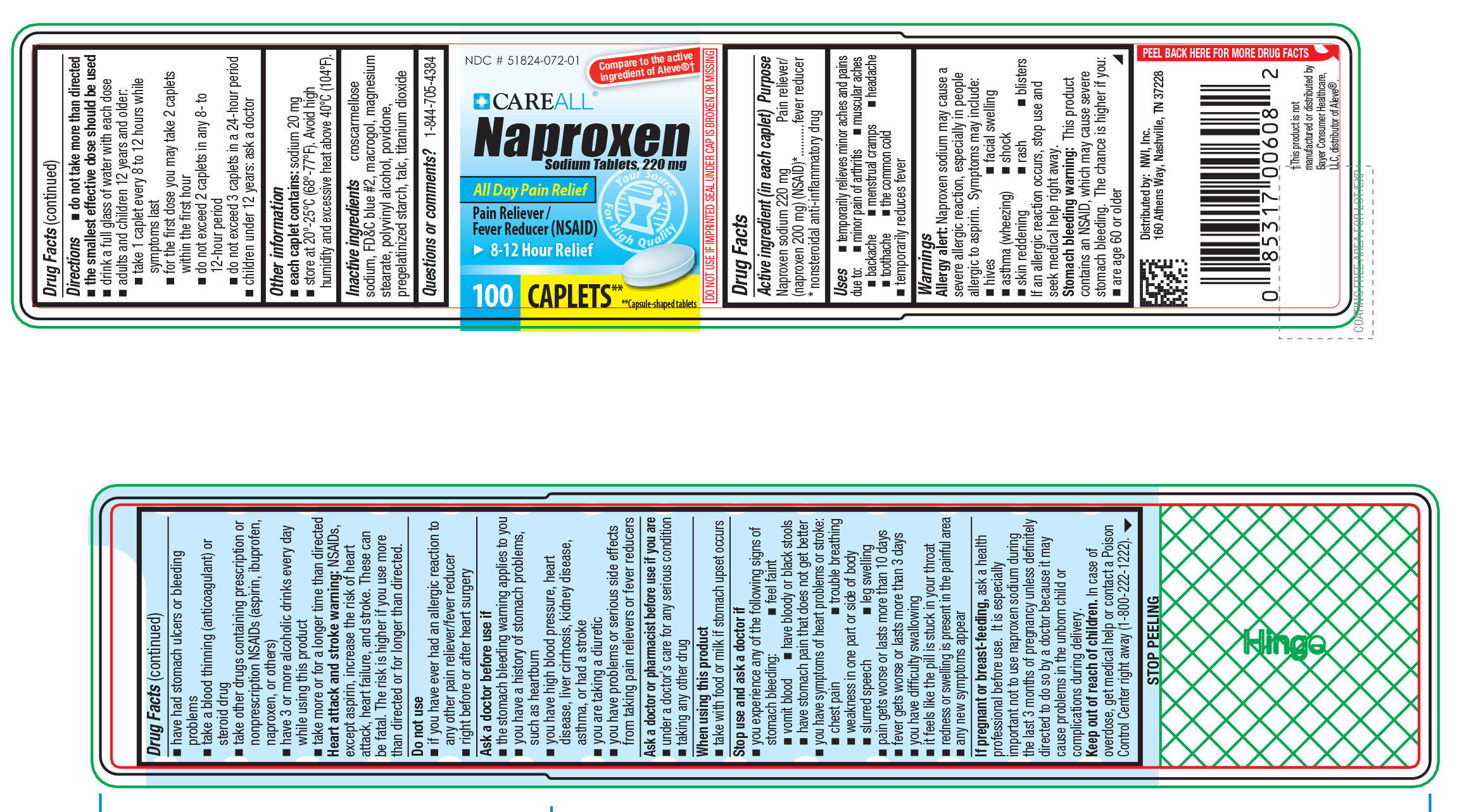 DRUG LABEL: CAREALL Naproxen
NDC: 51824-072 | Form: TABLET
Manufacturer: New World Imports, Inc.
Category: otc | Type: HUMAN OTC DRUG LABEL
Date: 20251201

ACTIVE INGREDIENTS: NAPROXEN SODIUM 220 mg/1 1
INACTIVE INGREDIENTS: CROSCARMELLOSE SODIUM; FD&C BLUE NO. 2; MAGNESIUM STEARATE; POVIDONE; TITANIUM DIOXIDE; STARCH, CORN; POLYETHYLENE GLYCOL, UNSPECIFIED; POLYVINYL ALCOHOL, UNSPECIFIED; TALC

Active ingredients (in each caplet)

Active ingredient (in each caplet)

Naproxen sodium 220mg

(Naproxen 200mg) (NSAID)*

*nonsteroidal anti-inflammatory drug

Purpose

Pain reliever / fever reducer

Uses

Temporarily relieves minor aches and pains due to: minor pain of arthritis, backache, headache, muscular aches, menstrual cramps, toothache, common cold, temporarily reduces fever

Warnings

Allergy alert:Naproxen sodium may cause a severe allergic reaction, especially in people allergic to aspirin. Symptoms may include hives, facial swelling, asthma(wheezing), shock, skin reddening, rash, blisters. If an allergic reaction occurs, stop use and seek medical help right away

Stomach bleeding warning: This product contains NSAID, which may casue severe stomach bleeding. The chance is higher if you are age 60 or older, have had stomach ulcers or bleeding problems, take a blood thinning (anticoagulant) or steroid drug, take other drugs containing prescription or nonprescription NSAIDs (aspirin, ibuprofen, naproxen, or others), have 3 or more alcoholic drinks everyday while using this product, take more or for a longer time than directed.

Heart attack and stroke warning: NSAIDs, except aspirin, increase the rist of heart attack, heart failure and stroke. These can be fatal. The risk is higher if you use more than directed or for longer than directed.

Do Not Use:

If you have ever had an allergic reaction to any other pain reliever/fever reducer

Right before or after heart surgery

Do not use

If you have ever had an allergic reaction to any other pain reliever/fever reducer.

Right before or after heart surgery

When using this product

Take with food or milk if stomach upset occurs.

Ask a doctor before use if:

The stomach bleeding warning applies to you

You ahve a history of stomach problems, such as heartburn

You have high blood pressure, heart disease, liver cirrhosis, kidney disease, asthma or had a stroke

You are taking a diuretic

You have problems or serious side effects from taking pain relievers or fever reducers

Ask a doctor or pharmacist before use if you are:

Under a doctor's care for any serious condition

Taking any other drugs

Stop use and ask a doctor if:

You experience any of the following signs of stomach bleeding: you feel faint, vomit blood, have bloddy or black stools, have stomach pain that does not get better

You have symptoms of heart problems or stroke, chest pain, trouble breathing, weakness in one part or side of body, slurred speech, or leg swelling

Pain gets worse or lasts more than 10 days

Fever gets worse or lasts more than 3 days

You have difficulty swallowing

It feels like the pill is stuck in your throat

redness or swelling is present in the painful area

Any new symptoms appear

If pregnant or breast-feeding,ask a health professional before use. It is especially important not to use naproxen sodium during the last 3 months of pregnancy unless definately directed to do so by a doctor because it may cause problems in the unborn child or complications during delivery

Keep out of reach of children. In case of overdose, get medical help or contact a Poison Control Center immediately (1-800-222-1222).

Directions

Do not take more than directed. The smallest effective dose should be used. Drink a full glass of water with each dose

Adults and children 12 years and older:

- Take 1 caplet every 8 to 12 hours while symptoms last
- For the first dose you may take 2 caplets within the first hour
- Do not exceed 2 caplets in any 8 - 12 hour period
- Do not exceed 3 caplets in a 24 hour period

Children under 12 years:ask a doctor

Inactive ingredients

croscarmellose sodium, FD&C blue number 2, macrogol, magnesium stearate, polyvinyl alcohol, povidone, pregelatinized starch, talc, titanium dioxide